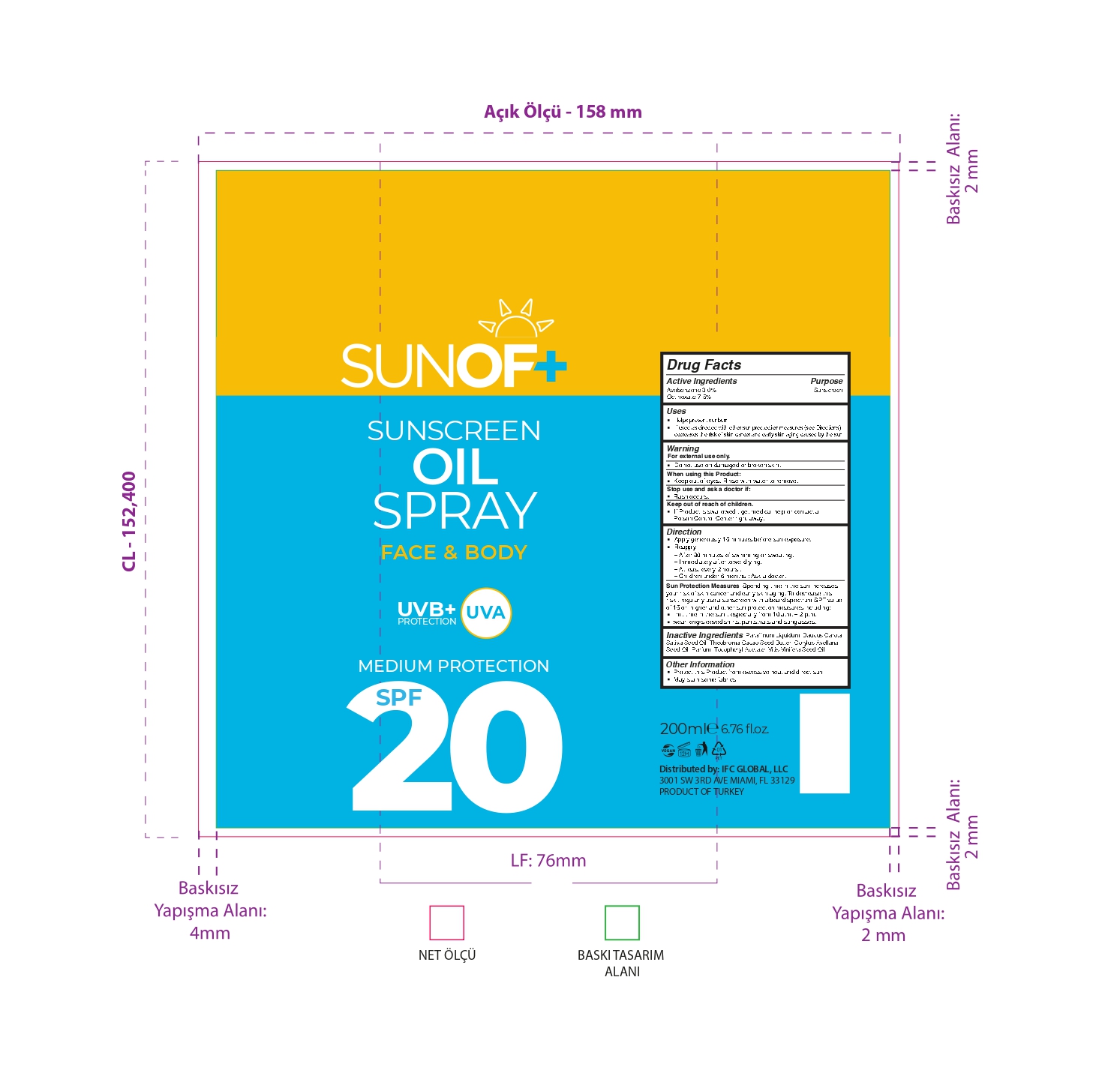 DRUG LABEL: SUNOF Sun Oil SPF 20
NDC: 77418-004 | Form: SPRAY
Manufacturer: ATAK FARMA KOZMETIK VE KIMYA SANAYI TICARET ANONIM SIRKETI
Category: otc | Type: HUMAN OTC DRUG LABEL
Date: 20250105

ACTIVE INGREDIENTS: AVOBENZONE 3 g/100 mL; OCTINOXATE 7.5 g/100 mL
INACTIVE INGREDIENTS: CORYLUS AVELLANA (HAZELNUT) SEED OIL; VITIS VINIFERA (GRAPE) SEED OIL; DAUCUS CAROTA SATIVA (CARROT) SEED OIL; PARAFFINUM LIQUIDUM; .ALPHA.-TOCOPHEROL ACETATE, DL-; THEOBROMA CACAO (COCOA) SEED BUTTER; PARFUMIDINE

Inactive Ingredients

Paraffinum Liquidum, Daucus Carota

Sativa Seed Oil, Theobroma Cacao Seed Butter, Corylus Avellana

Seed Oil, Parfum, Tocopheryl Acetate, Vitis Vinifera Seed Oil.

Warning

For external use only.

Do not use on damaged or broken skin.

When using this Product:

Keep out of eyes. Rinse with water to remove.

Active Ingredients

Avobenzone 3.0%

Octinoxate 7.5%

Other Safety Information

Stop use and ask a doctor if:

Rash occurs.

Keep out of reach of children

If Product is swallowed , get medical help or contact a

Poison Control Center right away.

Direction

Apply generously 15 minutes before sun exposure.

Reapply

Protect this Product from excessive heat and direct sun

May stain some fabrics

– After 80 minutes of swimming or sweating.

– Immediately after towel drying.

– At least every 2 hours .

– Children under 6 months : Ask a doctor.

Uses

Helps prevent sunburn

If used as directed with other sun proctection measures (see Directions),

decreases the risk of skin cancer and early skin aging caused by the sun.

Purpose

Sunscreen